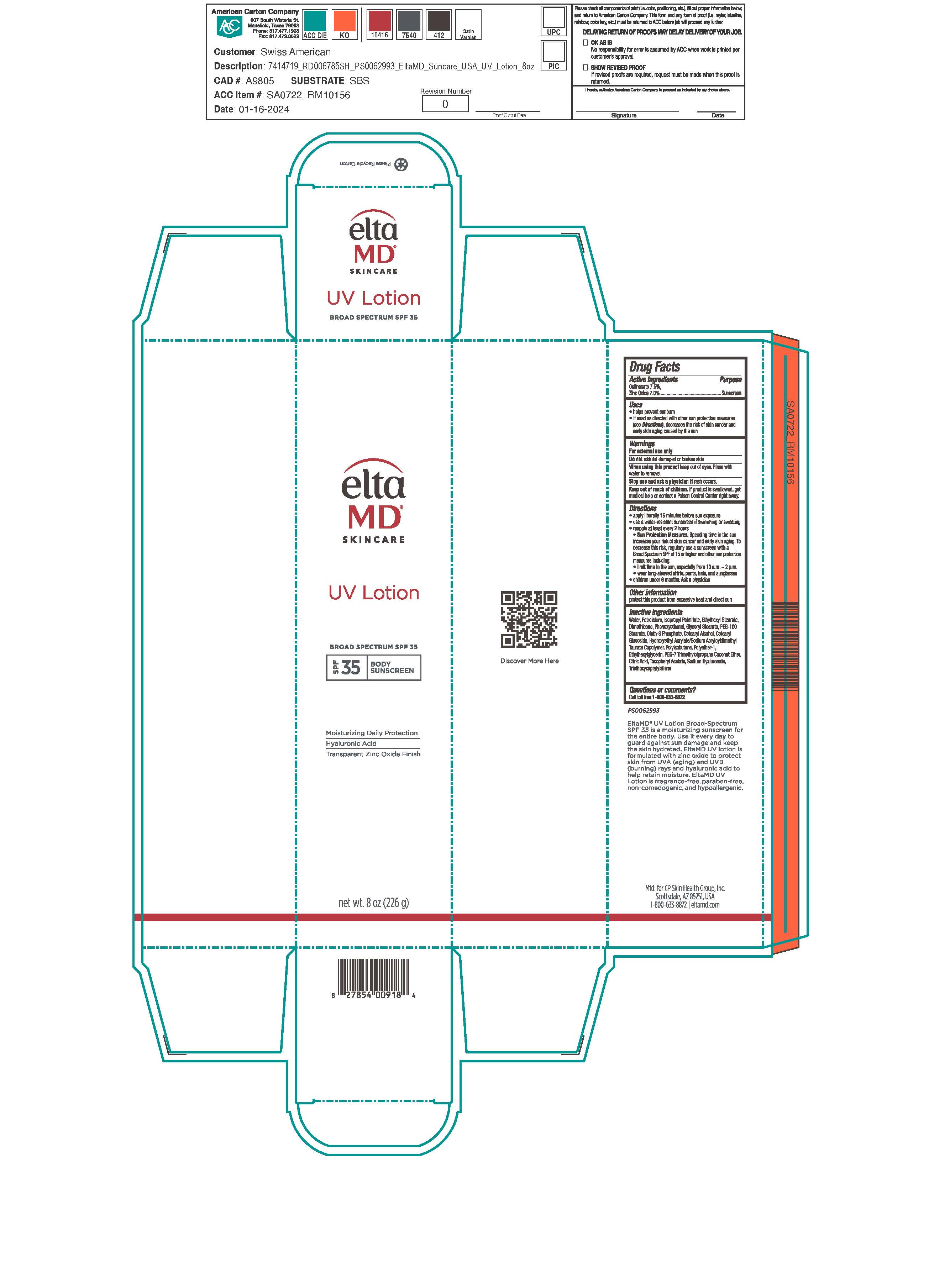 DRUG LABEL: EltaMD UV SPF35
NDC: 72043-6808 | Form: LOTION
Manufacturer: CP Skin Health Group, Inc
Category: otc | Type: HUMAN OTC DRUG LABEL
Date: 20251219

ACTIVE INGREDIENTS: ZINC OXIDE 70 g/1000 g; OCTINOXATE 75 g/1000 g
INACTIVE INGREDIENTS: WATER; PHENOXYETHANOL; ETHYLHEXYLGLYCERIN; PETROLATUM; DIMETHICONE; ISOPROPYL PALMITATE; OCTYL STEARATE; OLETH-3 PHOSPHATE; CETOSTEARYL ALCOHOL; CETEARYL GLUCOSIDE; GLYCERYL STEARATE/PEG-100 STEARATE; CITRIC ACID MONOHYDRATE; .ALPHA.-TOCOPHEROL ACETATE; HYALURONIC ACID; POLYISOBUTYLENE (1000 MW); HYDROXYETHYL ACRYLATE/SODIUM ACRYLOYLDIMETHYL TAURATE COPOLYMER (100000 MPA.S AT 1.5%); PEG-7 TRIMETHYLOLPROPANE COCONUT ETHER

EltaMD UV SPF35

Warnings

For external use only. Do not use on damaged or broken skin. When using this product keep out of eyes. Rinse with water to remove. Stop use and ask a physician if rash occurs. If product is swallowed get medical help or contact a Poison Control Center right away.

Active ingredients

Octinoxate 7.5% Sunscreen
Zinc Oxide 9.0% Sunscreen

Indications & Uses:

Helps prevent sunburn. If used as directed with other sun protection measure (See Directions), decreases the risk of skin cancer and early skin aging caused by the sun.

Indications & Uses:

Helps prevent sunburn. If used as directed with other sun protection measure (See Directions), decreases the risk of skin cancer and early skin aging caused by the sun.

Keep out of reach of children

Directions

Apply liberally 15 minutes before sun exposure. Use a water-resistant sunscreen if swimming or sweating. Reapply at least every 2 hours. Sun Protection Measures: Spending time in the sun increases your risk of skin cancer and early skin aging. To decrease this risk, regularly use a sunscreen with a broad-spectrum SPF of 15 or higher and other sun protection measures including: limit time in the sun, especially from 10 am to 2 pm. Wear long-sleeve shirts, pants, hats, and sunglasses. Children under 6 months: ask a physician.

Other information:

Protect this product from excessive heat and direct sun.

Inactive ingredients

water, petrolatum, isopropyl palmitate, ethylhexyl stearate, dimethicone, phenoxyethanol, glyceryl stearate, PEG-100 stearate, oleth-3 phosphate, cetearyl alcohol, cetearyl glucoside, hydroxyethyl acrylate/sodium acryloyldimethyl taurate copolymer, polyisobutene, polyether-1, ethylhexylglycerin, PEG-7 trimethylolpropane coconut ether, citric acid, tocopheryl acetate, sodium hyaluronate, triethoxycaprylylsilane

Questions?

Call toll free 1-800-633-8872